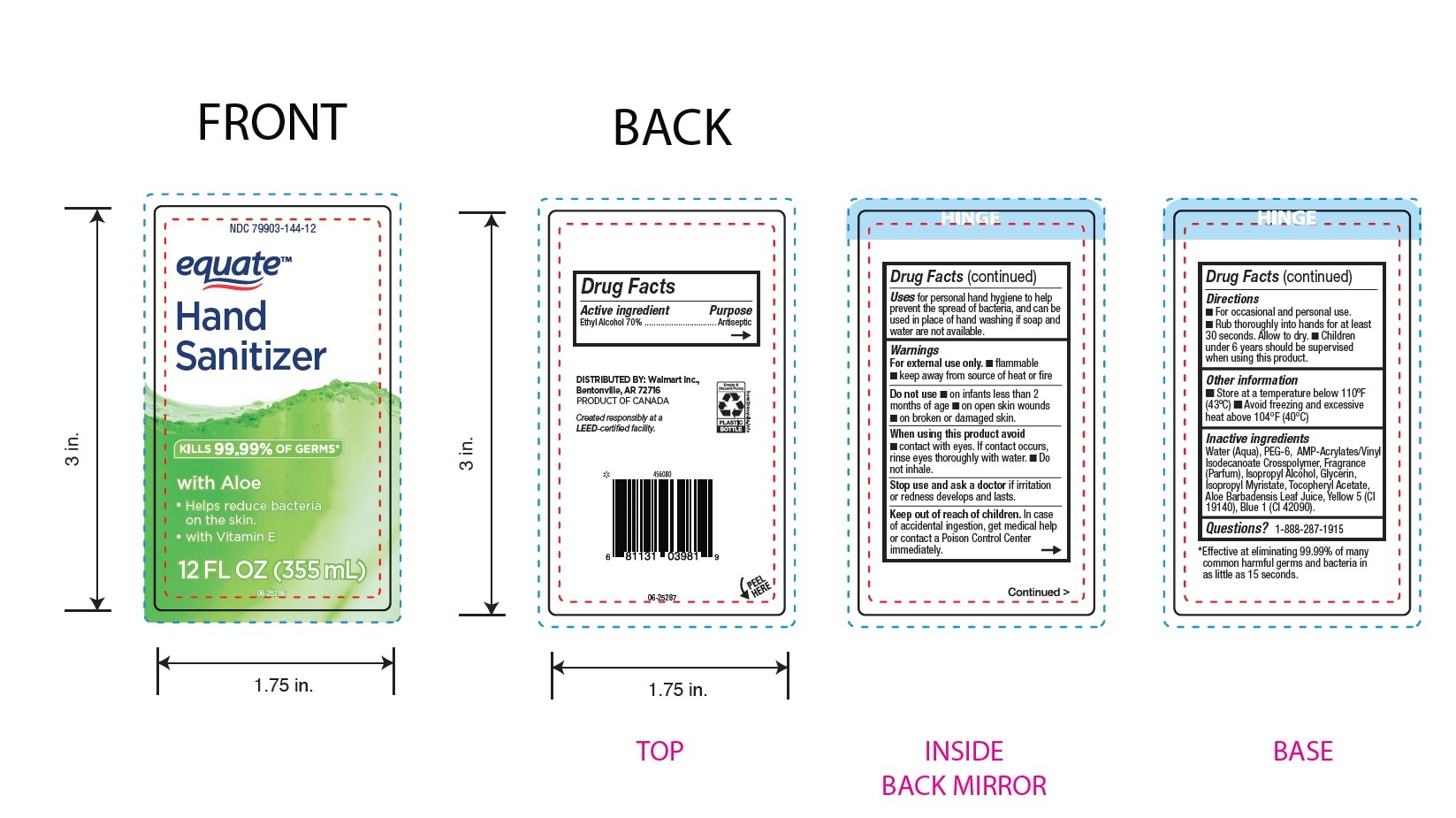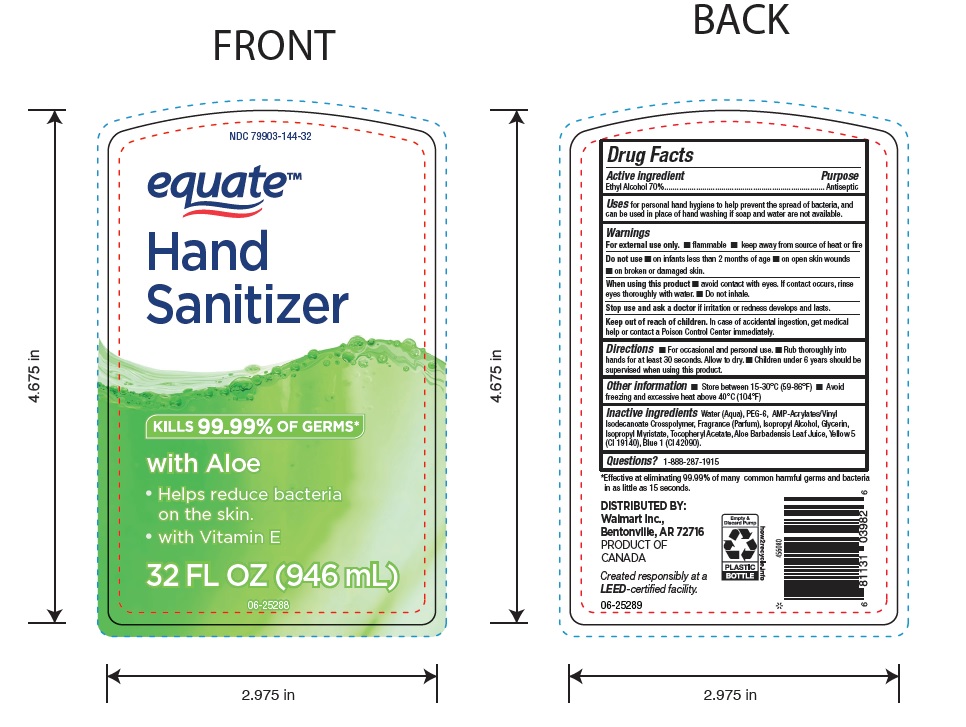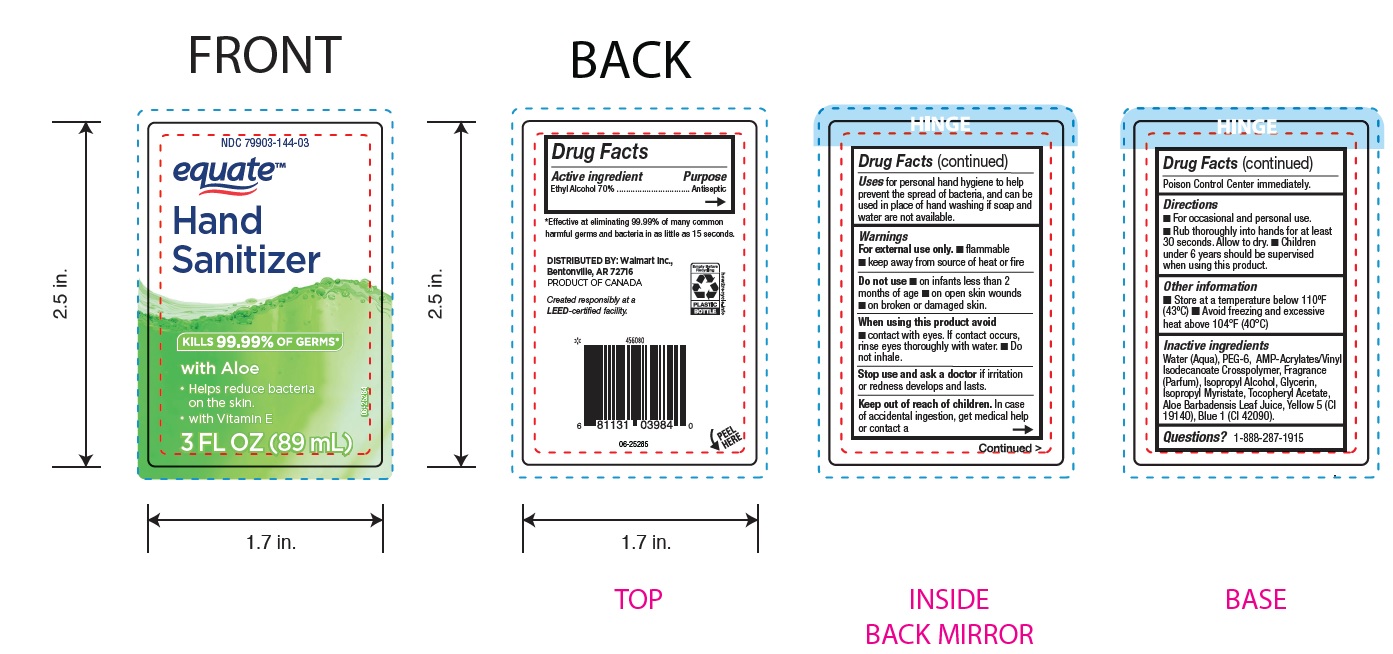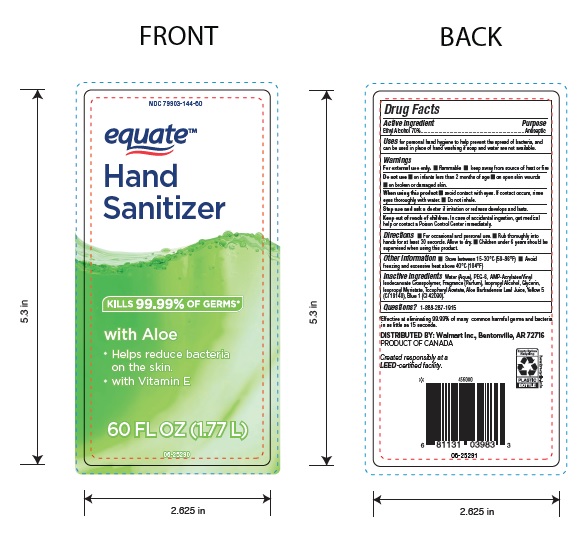 DRUG LABEL: Equate
NDC: 79903-144 | Form: GEL
Manufacturer: Wal-Mart Stores Inc.
Category: otc | Type: HUMAN OTC DRUG LABEL
Date: 20250201

ACTIVE INGREDIENTS: ALCOHOL 700 mg/1 mL
INACTIVE INGREDIENTS: ACRYLATES/VINYL ISODECANOATE CROSSPOLYMER (10000 MPA.S NEUTRALIZED AT 0.5%); FRAGRANCE CLEAN ORC0600327; ISOPROPYL MYRISTATE; GLYCERIN; .ALPHA.-TOCOPHEROL ACETATE; WATER; PEG-6; HC YELLOW NO. 5; DIRECT BLUE 1; ALOE VERA LEAF; ISOPROPYL ALCOHOL

WalMart sanitizer-79903-144

ACTIVE INGREDIENT

Ethyl Alcohol 70%

PURPOSE

Antiseptic

WARNINGS

For external use only. ■ Flammable ■ Keep away from source of heat or fire.

Do not use ■ on infants less than 2 months of age ■ on open skin wounds
■ on broken or damaged skin.

WHEN USING

■ avoid contact with eyes. If contact occurs, rinse eyes thoroughly with water. ■ Do not inhale.

Stop use and ask a doctorif irritation or redness develops and lasts.

Keep out of reach of children. In case of accidental ingestion, get medical help or contact a Poison Control Center immediately.

DOSAGE AND ADMINISTRATION

■ For occasional and personal use. ■ Rub thoroughly into hands for at least 30 seconds. Allow to dry. ■ Children under 6 years should be supervised when using this product.

INDICATIONS AND USAGE

For personal hand hygiene to help prevent the spread of bacteria, and can be used in place of hand washing if soap and

water are not available.

STORAGE AND HANDLING

■ Store at a temperature below 110ºF (43ºC) ■ Avoid freezing and excessive heat above 104°F (40°C)

INACTIVE INGREDIENT

Water (Aqua), PEG-6, AMP-Acrylates/Vinyl Isodecanoate Crosspolymer, Fragrance (Parfum), Isopropyl Alcohol, Glycerin,
Isopropyl Myristate, Tocopheryl Acetate, Aloe Barbadensis Leaf Juice, Yellow 5 (Cl 19140), Blue 1 (Cl 42090).